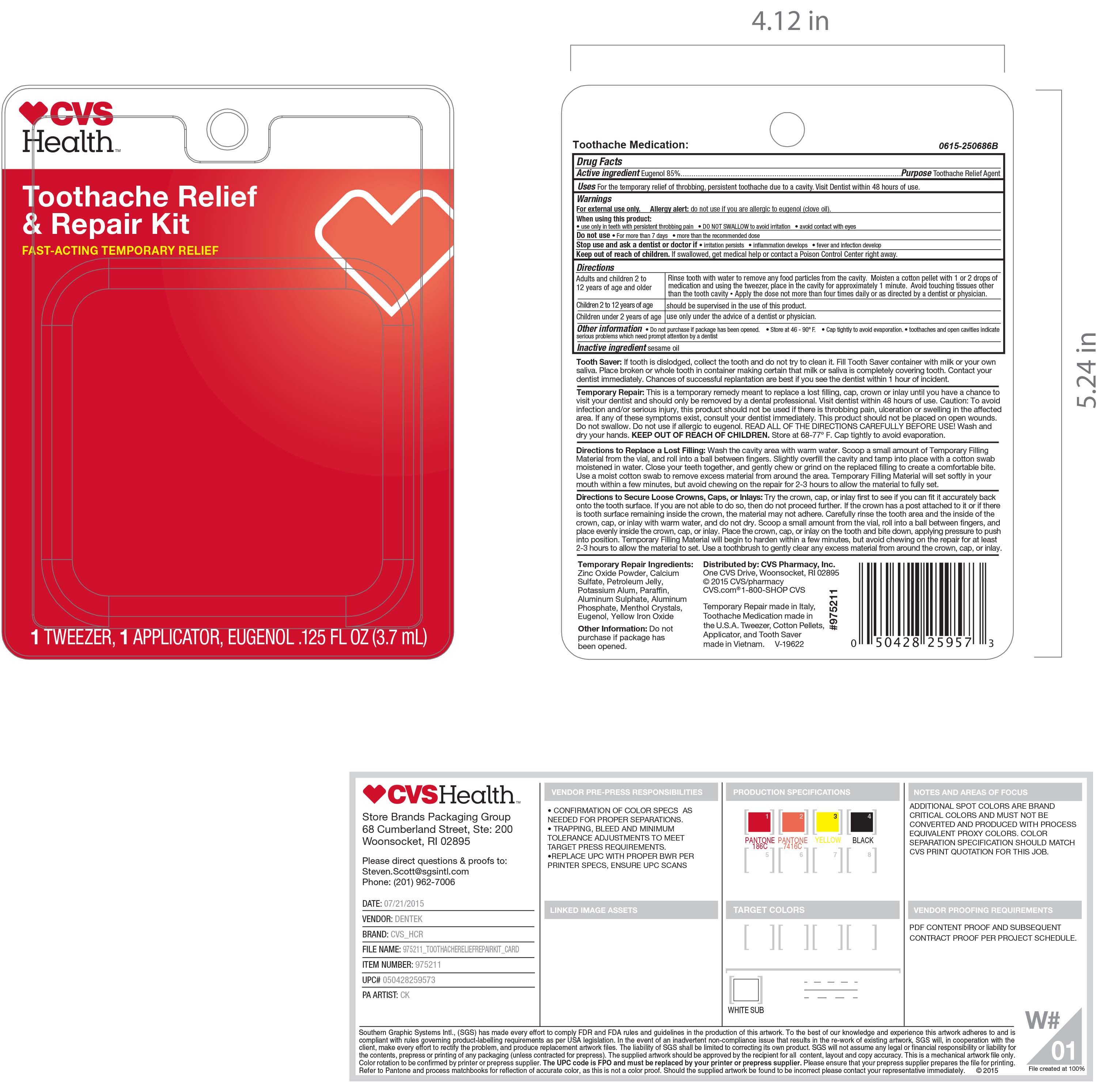 DRUG LABEL: Eugenol Toothache Medication
NDC: 67659-415 | Form: LIQUID
Manufacturer: Team Technologies, Inc
Category: otc | Type: HUMAN OTC DRUG LABEL
Date: 20211228

ACTIVE INGREDIENTS: EUGENOL 850 mg/1 mL
INACTIVE INGREDIENTS: SESAME OIL 150 mg/1 mL

CVS TOOTHACHE RELIEF & REPAIR KIT (Prestige)

Active Ingredient Eugenol 85%

Purpose Toothache Relief Agent

INDICATIONS AND USAGE

Uses For the temporary relief of throbbing, persistent toothache due to a cavity. Visit Dentist within 48 hours of use.

Warnings

For external use only. Allergy alert: do not use if you are allergic to eugenol (clove oil).

When using this product:

. use only in teeth with persistent throbbing pain . DO NOT SWALLOW to avoid irritation . avoid contact with eyes

Do not use. For more than 7 days . more than the recommended dose

Stop use and ask a dentist or doctor if. irritation persists . inflammation develops . fever and infection develop

Keep out of reach of children. If swallowed, get medical help or contact a Poison Control Center right away.

Directions

Adults and children 2 to 12 years of age and older: Rinse tooth with water to remove any food particles from the cavity. Moisten a cotton pellet with 1 or 2 drops of medication and using the tweezer, place in the cavity for approximately 1 minute. Avoid touching tissues other than the tooth cavity . Apply the dose not more than four times daily or as directed by a dentist or physician.

Children 2 to 12 years of age: should be supervised in the use of this product.

Children under 2 years of age: use only under the advice of a dentist or physician.

Other information. Do not purchase if package has been opened. . Store at 46 - 90o F. . Cap tightly to avoid evaporation. . toothaches and open cavities indicate serious problems which need prompt attention by a dentist.

Inactive ingredient sesame oil